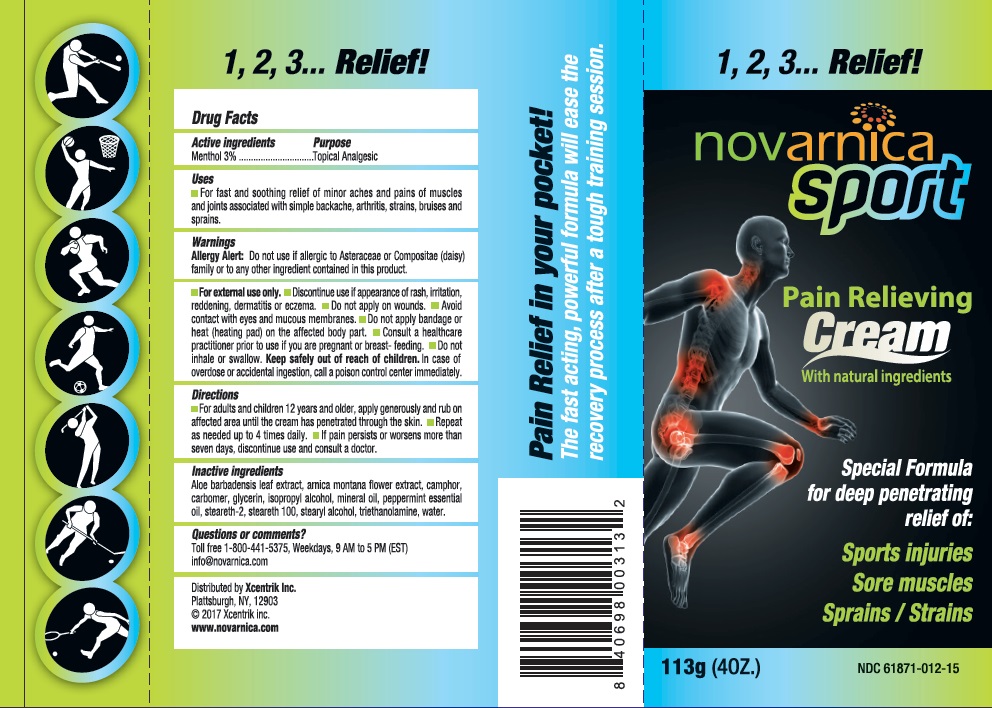 DRUG LABEL: Novarnica Sport
NDC: 61871-012 | Form: CREAM
Manufacturer: Xcentrik Inc.
Category: otc | Type: HUMAN OTC DRUG LABEL
Date: 20221219

ACTIVE INGREDIENTS: MENTHOL 3 g/100 g
INACTIVE INGREDIENTS: ALOE VERA LEAF; ARNICA MONTANA FLOWER; CAMPHOR (NATURAL); CARBOMER HOMOPOLYMER TYPE C (ALLYL PENTAERYTHRITOL CROSSLINKED); GLYCERIN; ISOPROPYL ALCOHOL; MINERAL OIL; PEPPERMINT OIL; STEARETH-2; STEARETH-100; STEARYL ALCOHOL; TROLAMINE; WATER

Drug Facts

Active ingredients

Menthol 3%

Purpose

Topical Analgesic

Uses

For fast and soothing relief of minor aches and pains of muscles and joints associated with simple backache, arthritis, strains, bruises and sprains.

Warnings

Allergy Alert: Do not use if allergic to Asteraceae or Compositae (daisy) family or to any other ingredient contained in this product.

- For external use only.
- Discontinue use if appearance of rash, irritation, reddening, dermatitis or eczema.
- Do not apply on wounds.
- Avoid contact with eyes and mucous membranes.
- Do not apply bandage or heat (heating pad) on the affected body part.
- Consult a healthcare practitioner prior to use if you are pregnant or breast-feeding.
- Do not inhale or swallow.

KEEP OUT OF REACH OF CHILDREN

- Keep safely out of reach of children. In case of overdose or accidental ingestion, call a poison control center immediately.

Directions

- For adults and children 12 years and older, apply generously and rub on affected area until the cream has penetrated through the skin.
- Repeat as needed up to 4 times daily.
- If pain persists or worsens more than seven days, discontinue use and consult a doctor.

Inactive ingredients

Aloe barbadensis leaf extract, arnica montana flower extract, camphor, carbomer, glycerin, isopropyl alcohol, mineral oil, peppermint essential oil, steareth-2, steareth-100, stearyl alcohol, triethanolamine, water.

Questions or comments?

Toll free 1-800-441-5375, Weekdays, 9 AM to 5 PM (EST)
info@novarnica.com

Distributed by Xcentrik Inc.
Plattsburgh, NY, 12903
© 2017 Xcentrik Inc.
www.novarnica.com

Principal Display Panel

novarnica sport

Pain Relieving
Cream
With natural ingredients

Special formula
for deep penetrating
relief of:

Sports injuries
Sore muscles
Sprains/Strains

113g (4OZ.) NDC 61871-012-15